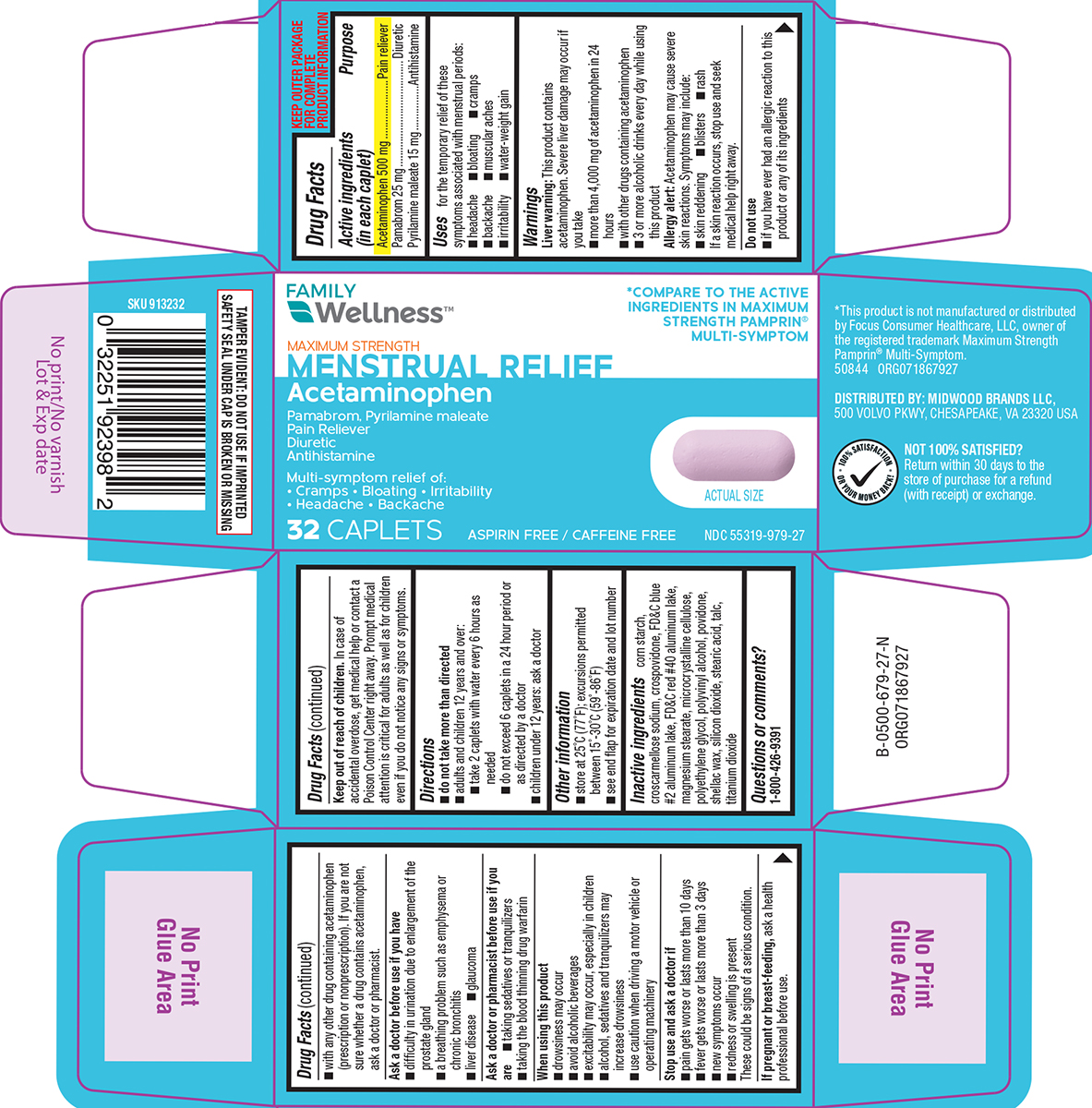 DRUG LABEL: Menstrual Relief
NDC: 55319-979 | Form: TABLET, FILM COATED
Manufacturer: Family Dollar Services Inc
Category: otc | Type: HUMAN OTC DRUG LABEL
Date: 20260107

ACTIVE INGREDIENTS: ACETAMINOPHEN 500 mg/1 1; PAMABROM 25 mg/1 1; PYRILAMINE MALEATE 15 mg/1 1
INACTIVE INGREDIENTS: STARCH, CORN; CROSCARMELLOSE SODIUM; CROSPOVIDONE, UNSPECIFIED; FD&C BLUE NO. 2 ALUMINUM LAKE; FD&C RED NO. 40 ALUMINUM LAKE; MAGNESIUM STEARATE; MICROCRYSTALLINE CELLULOSE; POLYETHYLENE GLYCOL, UNSPECIFIED; POLYVINYL ALCOHOL, UNSPECIFIED; POVIDONE, UNSPECIFIED; SHELLAC; SILICON DIOXIDE; STEARIC ACID; TALC; TITANIUM DIOXIDE

Family Wellness 44-679

Active ingredients (in each caplet)

Acetaminophen 500 mg
Pamabrom 25 mg
Pyrilamine maleate 15 mg

Purpose

Pain reliever
Diuretic
Antihistamine

Uses

for the temporary relief of these symptoms associated with menstrual periods:

- headache
- bloating
- cramps
- backache
- muscular aches
- irritability
- water-weight gain

Warnings

Liver warning: This product contains acetaminophen. Severe liver damage may occur if you take

- more than 4,000 mg of acetaminophen in 24 hours
- with other drugs containing acetaminophen
- 3 or more alcoholic drinks every day while using this product

Allergy alert: Acetaminophen may cause severe skin reactions. Symptoms may include:

- skin reddening
- blisters
- rash

If a skin reaction occurs, stop use and seek medical help right away.

Do not use

- with any other drug containing acetaminophen (prescription or nonprescription). If you are not sure whether a drug contains acetaminophen, ask a doctor or pharmacist.
- if you have ever had an allergic reaction to this product or any of its ingredients

Ask a doctor before use if you have

- difficulty in urination due to enlargement of the prostate gland
- a breathing problem such as emphysema or chronic bronchitis
- liver disease
- glaucoma

Ask a doctor or pharmacist before use if you are

- taking sedatives or tranquilizers
- taking the blood thinning drug warfarin

When using this product

- drowsiness may occur
- avoid alcoholic beverages
- excitability may occur, especially in children
- alcohol, sedatives and tranquilizers may increase drowsiness
- use caution when driving a motor vehicle or operating machinery

Stop use and ask a doctor if

- pain gets worse or lasts more than 10 days
- fever gets worse or lasts more than 3 days
- new symptoms occur
- redness or swelling is present

These could be signs of a serious condition.

If pregnant or breast-feeding,

ask a health professional before use.

Keep out of reach of children.

In case of accidental overdose, get medical help or contact a Poison Control Center right away. Prompt medical attention is critical for adults as well as for children even if you do not notice any signs or symptoms.

Directions

- do not take more than directed
- adults and children 12 years and over:
  - take 2 caplets with water every 6 hours as needed
  - do not exceed 6 caplets in a 24 hour period or as directed by a doctor
- children under 12 years: ask a doctor

Other information

- store at 25ºC (77ºF); excursions permitted between 15º-30ºC (59º-86ºF)
- see end flap for expiration date and lot number

Inactive ingredients

corn starch, croscarmellose sodium, crospovidone, FD&C blue #2 aluminum lake, FD&C red #40 aluminum lake, magnesium stearate, microcrystalline cellulose, polyethylene glycol, polyvinyl alcohol, povidone, shellac wax, silicon dioxide, stearic acid, talc, titanium dioxide

Questions or comments?

1-800-426-9391

Principal display panel

FAMILY
Wellness™

*COMPARE TO THE ACTIVE
INGREDIENTS IN MAXIMUM
STRENGTH PAMPRIN®
MULTI-SYMPTOM

MAXIMUM STRENGTH
MENSTRUAL RELIEF
Acetaminophen
Pamabrom, Pyrilamine maleate
Pain Reliever
Diuretic
Antihistamine

Multi-symptom relief of:
• Cramps • Bloating • Irritability
• Headache • Backache

32 CAPLETS

ASPIRIN FREE / CAFFEINE FREE

ACTUAL
SIZE

NDC 55319-979-27

TAMPER EVIDENT: DO NOT USE IF IMPRINTED
SAFETY SEAL UNDER CAP IS BROKEN OR MISSING

*This product is not manufactured or distributed
by Focus Consumer Healthcare, LLC, owner of
the registered trademark Maximum Strength
Pamprin® Multi-Symptom.
50844 ORG071867927

DISTRIBUTED BY: MIDWOOD BRANDS LLC,
500 VOLVO PKWY, CHESAPEAKE, VA 23320 USA

NOT 100% SATISFIED?
Return within 30 days to the
store of purchase for a refund
(with receipt) or exchange.

Family Wellness 44-679